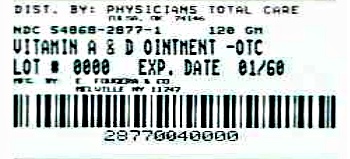 DRUG LABEL: Vitamin A and Vitamin D
NDC: 54868-2877 | Form: OINTMENT
Manufacturer: Physicians Total Care, Inc.
Category: otc | Type: HUMAN OTC DRUG LABEL
Date: 20120904

ACTIVE INGREDIENTS: PETROLATUM 929.3 mg/1 g
INACTIVE INGREDIENTS: LANOLIN; PARAFFIN; VITAMIN A PALMITATE; VITAMIN D

Vitamin A & Vitamin D Ointment

Active Ingredient:

White Petrolatum (929.3 mg)

Purpose:

Emollient

Uses:

- first aid in
- minor burns
- scalds
- sunburn
- windburn
- diaper rash
- chafing
- chapped skin
- nipple care
- abrasions
- cuts
- ulcers

Warnings:

For external use only.

Ask doctor before use if you have severe or extensive burns.

When using this product the treatment of ulcers, severe cuts or wounds should be under the direction of a doctor.

Keep out of reach of children.

If swallowed, get medical help or contact a Poison Control Center right away.

Directions:

- cleanse affected area with mild soap and warm water
- dry thoroughly
- apply Vitamin A & Vitamin D ointment in a thin layer to the affected area directly to the skin or by spreading on sterile gauze or clean cloth
- bandage loosely

Other information:

- do not use if seal is punctured or is not visible. To open, reverse cap to puncture seal
- store at room temperature
- see crimp of tube for Lot Number and Exp. Date

Inactive Ingredients

fragrance, lanolin, paraffin, vitamin A (as palmitate), vitamin D

Questions or comments? call toll free 1-800-645-9833

E. FOUGERA & CO.

A division of Fougera Pharmaceuticals Inc.

Melville, NY 11747

X5110C

R02/12

Distributed and "Additional barcode label" applied by:
Physicians Total Care, Inc.
Tulsa, Oklahoma 74146

PACKAGE LABEL – PRINCIPAL DISPLAY PANEL – CARTON

NDC 54868-2877-1

Vitamin A & Vitamin D Ointment (Emollient)

To promote healing of minor skin irritaions

NET WT 4 Oz